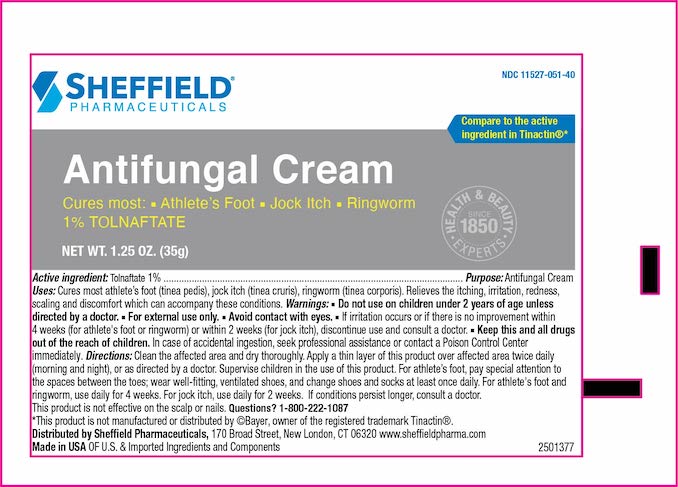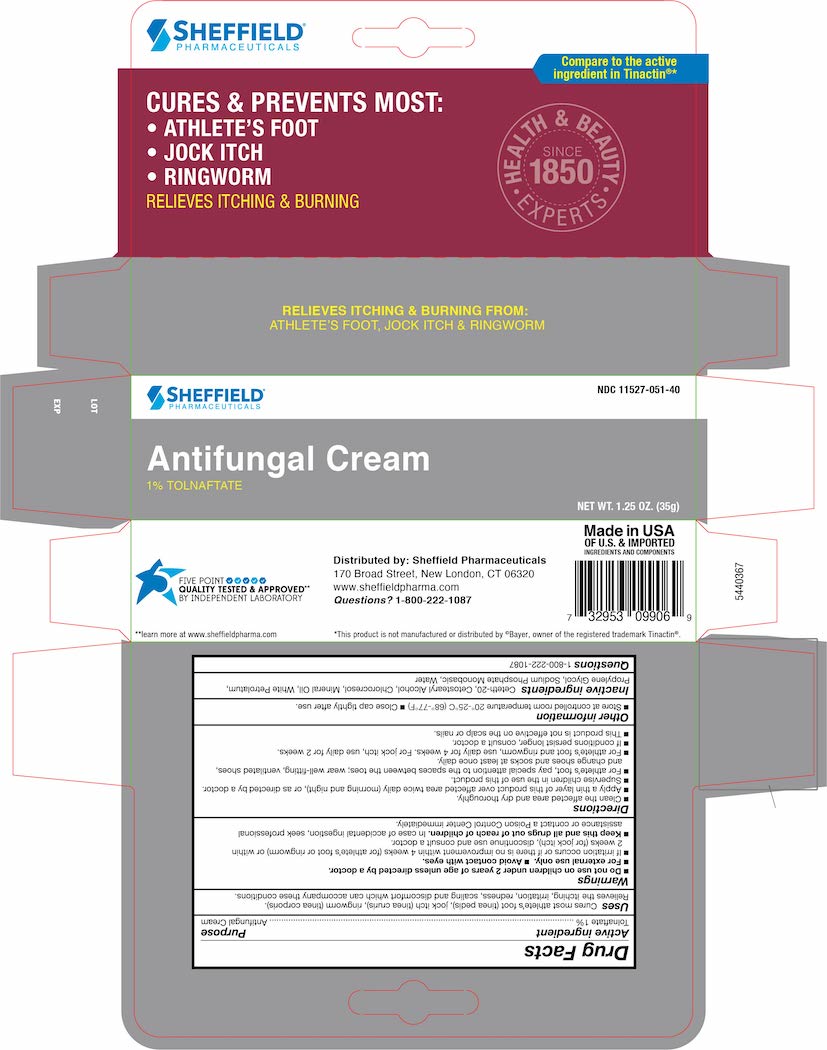 DRUG LABEL: Tolnaftate
NDC: 11527-051 | Form: CREAM
Manufacturer: Sheffield Pharmaceuticals LLC
Category: otc | Type: HUMAN OTC DRUG LABEL
Date: 20250220

ACTIVE INGREDIENTS: TOLNAFTATE 10 mg/1 g
INACTIVE INGREDIENTS: WATER; CETOSTEARYL ALCOHOL; CETETH-20; CHLOROCRESOL; MINERAL OIL; PETROLATUM; SODIUM PHOSPHATE, MONOBASIC, ANHYDROUS; PROPYLENE GLYCOL

Drug Facts

Active ingredient

Tolnaftate USP 1%

Purpose

Antifungal Cream

Uses

- Cures most athlete's foot (tinea pedis), jock itch (tinea cruris) and ringworm (tinea corporis).
- Relieves the itching, irratation, redness, scaling and discomfort which can accompany these conditions.

Warnings

- Do not use on children under 2 years of age unless directed by a doctor.
- For external use only avoid contact with eyes.
- Irritation occurs or if there is no improvement within 4 weeks (for athlete's foot and ringworm)irritation occurs or if there is no improvement within 2 weeks (for jock itch).

KEEP OUT OF REACH OF CHILDREN

Keep this and all drugs out of the reach of children.In case of accidental ingestion, seek professional assistance or contact a Poison Control Center immediately.

Directions

- Clean the affected area and dry thoroughly.
- Apply a thin layer of the product over the affected area twice daily (morning and night) or as directed by a doctor.
- Supervise children in the use of this product.

For athlete's foot

- Pay special attention to the spaces between the toes.
- Wear well fitting ventilated shoes.
- Change shoes and socks at least once daily.
- For athlete's foot and ringworm, use daily for 4 weeks.
- For jock itch, use daily for 2 weeks.
- If condition persists longer, consult a doctor.
- This product is not effective on the scalp or nails.

Other information

- Store at controlled room temperature 15°-30°C (59°-86°F).
- Close cap tighty after ever use.

Inactive ingredients

Ceteth-20, Cetostearyl Alcohol, Chlorocresol, Mineral Oil, White Petrolatum, Propylene Glycol, Sodium Phosphate Monobasic, Water

Questions?

1-800-222-1087

Principal Display Panel – 1.25 oz Tube

Dr. Sheffield's NDC 11527-051-40

1% Tolnafate

Antifungal Cream

CURES Most:

ATHLETE'S FOOT

JOCK ITCH

RINGWORM

Net Wt. 1.25 OZ (35.4 g)

Principal Display Panel – 1.25 oz Carton

Dr. Sheffield's NDC 11527-051-40

1% Tolnafate

Antifungal Cream

CURES Most:

ATHLETE'S FOOT

JOCK ITCH

RINGWORM

Net Wt. 1.25 OZ (35.4 g)